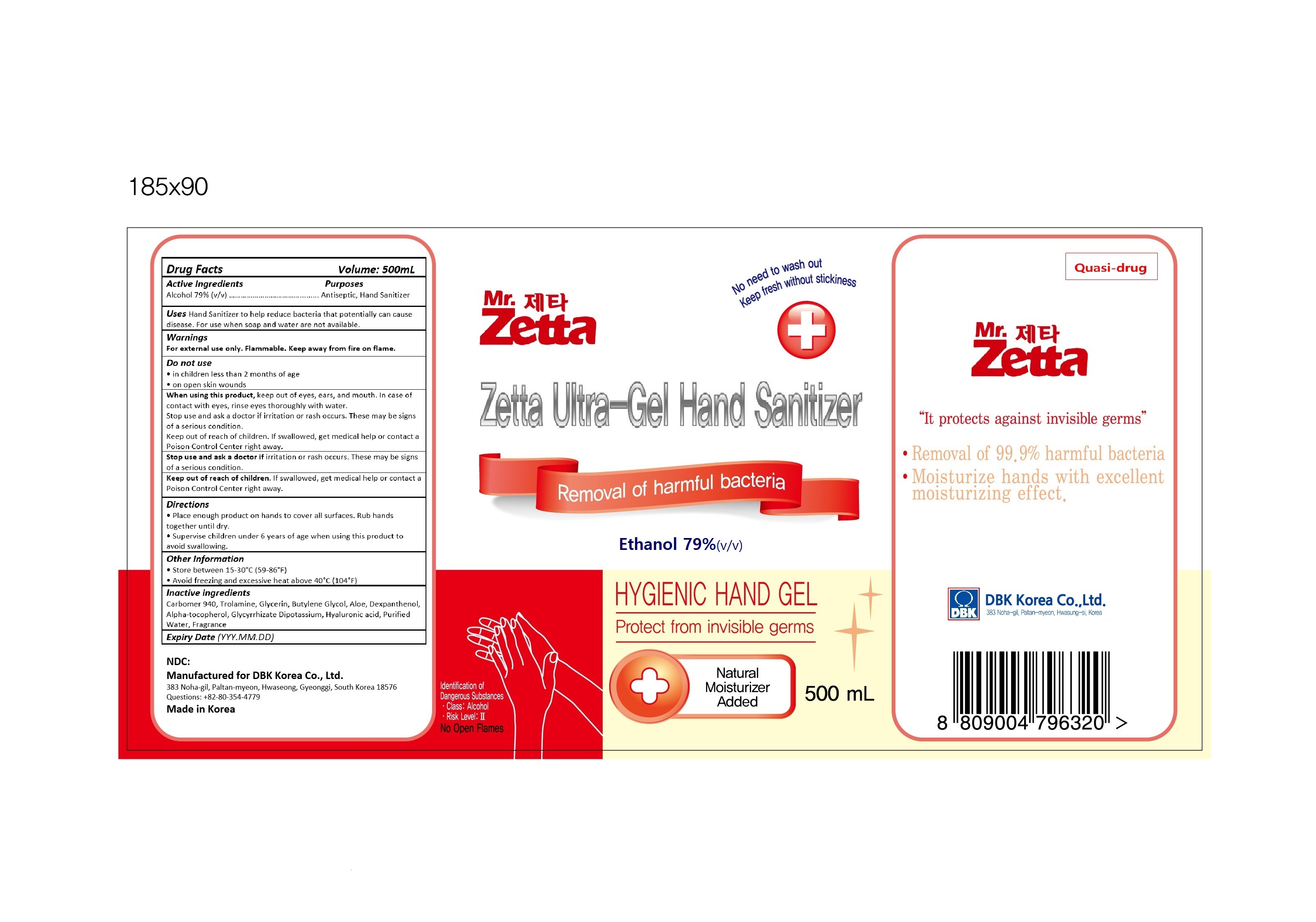 DRUG LABEL: Zetta Ultra-gel Hand Sanitizer
NDC: 74170-003 | Form: GEL
Manufacturer: DBK Korea Co., Ltd.
Category: otc | Type: HUMAN OTC DRUG LABEL
Date: 20200610

ACTIVE INGREDIENTS: ALCOHOL 79 mL/100 mL
INACTIVE INGREDIENTS: TROLAMINE; BUTYLENE GLYCOL; WATER; CARBOMER 940; GLYCERIN; ALPHA-TOCOPHEROL; ALOE; DEXPANTHENOL; GLYCYRRHIZINATE DIPOTASSIUM; HYALURONIC ACID

Zetta Ultra-gel Hand Sanitizer

Active Ingredient(s)

Alcohol 79% v/v. Purpose: Antiseptic

Purpose

Antiseptic, Hand Sanitizer

Use

Hand Sanitizer to help reduce bacteria that potentially can cause disease. For use when soap and water are not available.

Warnings

For external use only. Flammable. Keep away from heat or flame

Do not use

- in children less than 2 months of age
- on open skin wounds

When using this product keep out of eyes, ears, and mouth. In case of contact with eyes, rinse eyes thoroughly with water.
Stop use and ask a doctor if irritation or rash occurs. These may be signs of a serious condition.
Keep out of reach of children. If swallowed, get medical help or contact a Poison Control Center right away.

Stop use and ask a doctor if irritation or rash occurs. These may be signs of a serious condition.

Keep out of reach of children. If swallowed, get medical help or contact a Poison Control Center right away.

Directions

- Place enough product on hands to cover all surfaces. Rub hands together until dry.
- Supervise children under 6 years of age when using this product to avoid swallowing.

Other information

- Store between 15-30C (59-86F)
- Avoid freezing and excessive heat above 40C (104F)

Inactive ingredients

Carbomer 940, Trolamine, Glycerin, Butylene Glycol, Aloe, Dexpanthenol, Alpha-tocopherol, Glycyrrhizate Dipotassium, Hyaluronic acid, Purified Water, Fragrance

PACKAGE LABEL

500 mL NDC: 74170-003-01